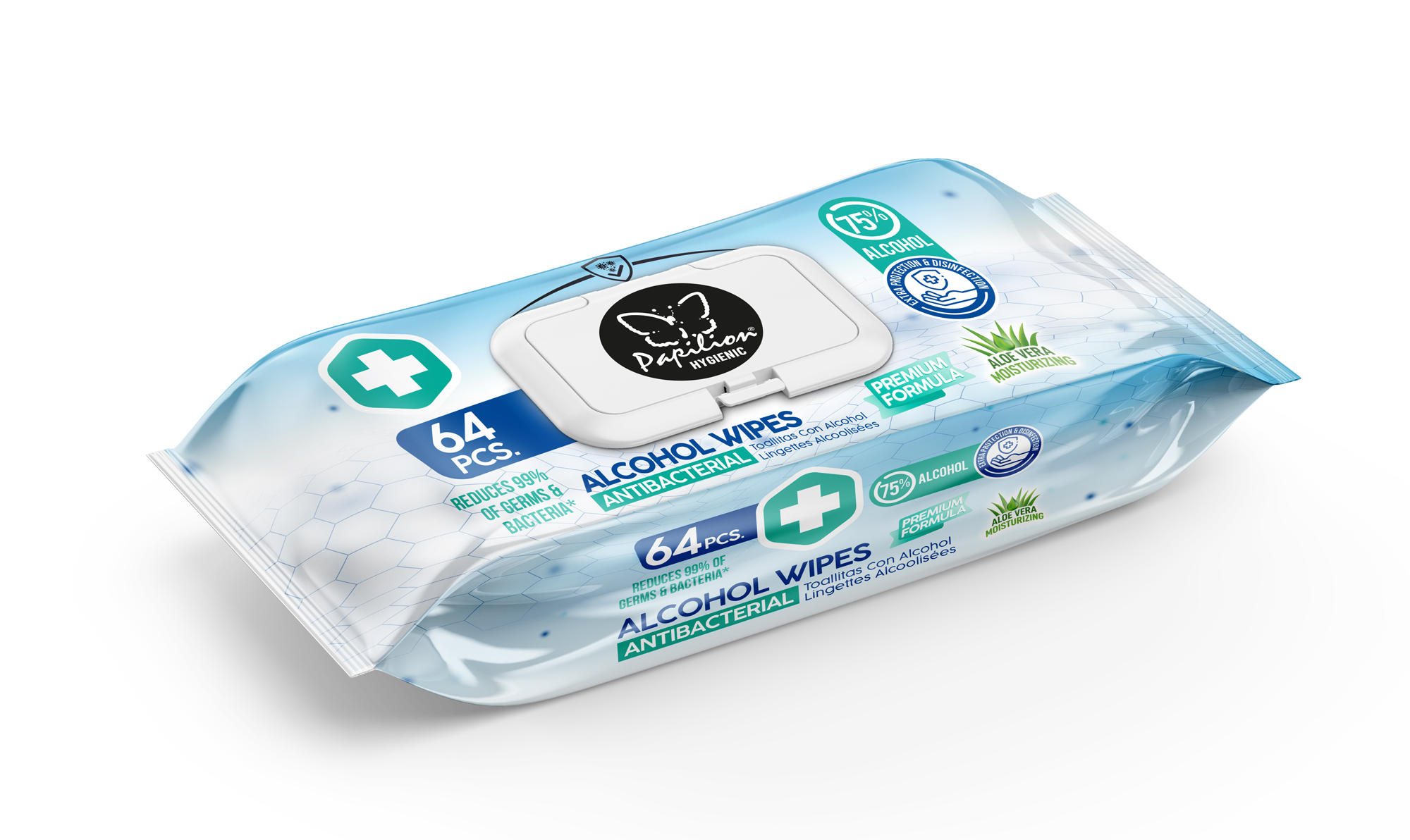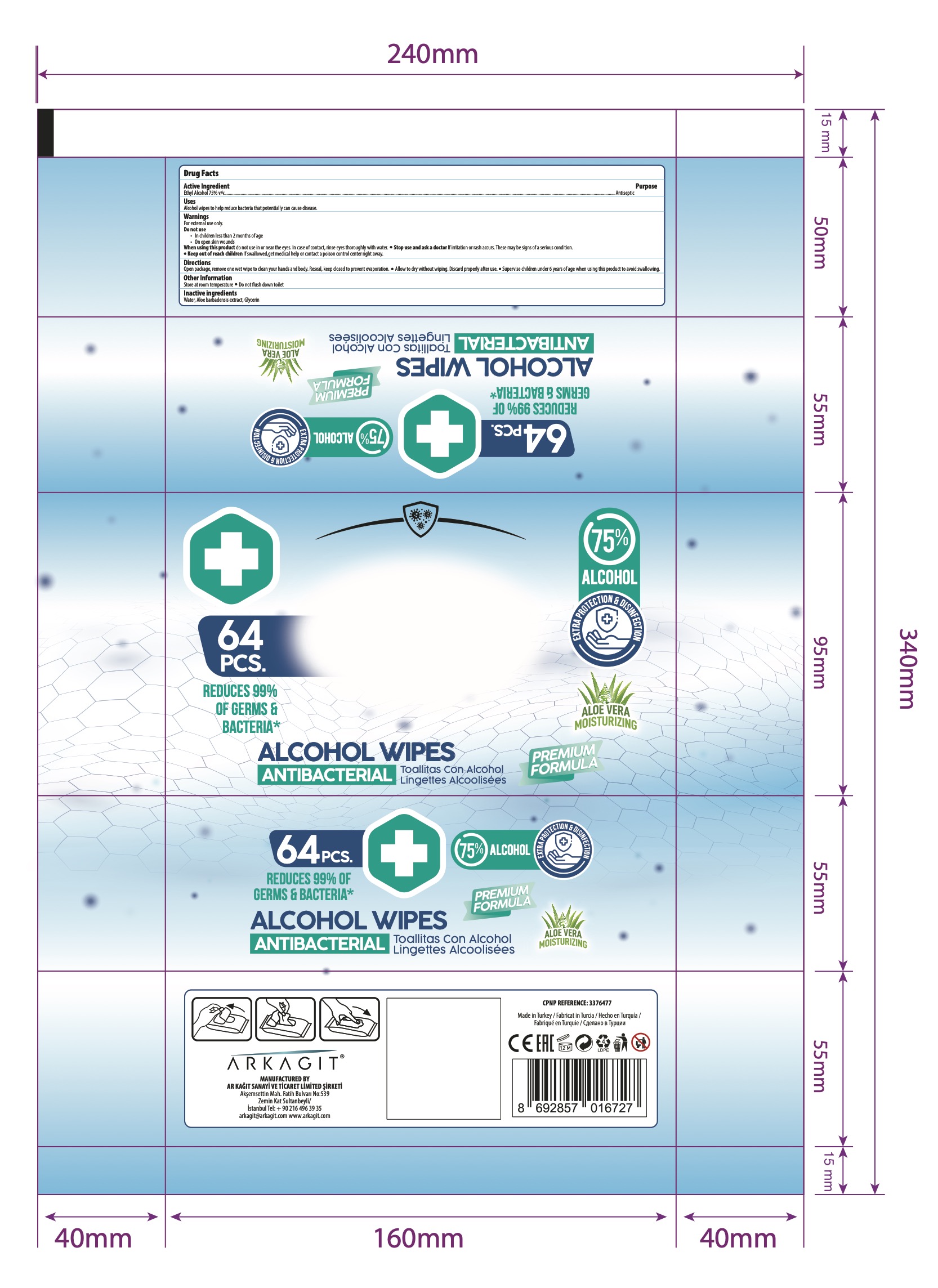 DRUG LABEL: PAPILION HYGIENIC ALCOHOL WIPES ANTIBACTERIAL
NDC: 79262-130 | Form: CLOTH
Manufacturer: AR KAGIT SAN. ve TIC. LTD. STI.
Category: otc | Type: HUMAN OTC DRUG LABEL
Date: 20210308

ACTIVE INGREDIENTS: ALCOHOL 75 mL/100 mL
INACTIVE INGREDIENTS: WATER 24.4 mL/100 mL; GLYCERIN 0.5 mL/100 mL; ALOE ARBORESCENS LEAF 0.1 mL/100 mL

Papilion HYGIENIC ALCOHOL WIPES

ANTIBACTERIAL

EXTA PROTECTION AND CLEANING

REDUCE 99% OF GERMS & BACTERIA

This is a hand sanitizer manufactured according to the Temporary Policy for Preparation of Certain Alcohol-Based Hand Sanitizer Products During the Public Health Emergency (CoViD-19); Guidance for Industry.

The hand sanitizer is manufactured using only the following United States Pharmacopoeia (USP) grade ingredients in the preparation of the product (percentage in final product formulation) consistent with World Health Organization (WHO) recommendations:

1. Alcohol (ethanol) (USP or Food Chemical Codex (FCC) grade) (75%, volume/volume (v/v)) in an aqueous solution denatured according to Alcohol and Tobacco Tax and Trade Bureau regulations in 27 CFR part 20.

2. ALOE BARBADENSIS EXTRCT (0.1 % v/v).
3. GLYCERIN (0.5 % v/v).
4. Sterile distilled water or boiled cold water.

The firm does not add other active or inactive ingredients. Different or additional ingredients may impact the quality and potency of the product.

Active Ingredient(s)

Alcohol 75% v/v. Purpose: Antiseptic/ Antiviral

Purpose

Papilion HYGIENIC ALCOHOL WIPES

ANTIBACTERIAL

Uses

Alcohol wipes to help reduce bacteria that potentially can cause disease.

Warnings

For external use only.

Do not use

in children less than 2 months of age

On open skin wounds

When using this product, do not use in or near the eyes. In case of contact, rinse eyes thoroughly with water.

Keep out of reach of children. If swallowed, get medical help or contact a Poison Control Center right away.

When using this product, do not use in or near the eyes. In case of contact, rinse eyes thoroughly with water.

Stop use and ask a doctor if irritation or rash develops and continues for more than 72 hours.

Keep out of reach of children. If swallowed, get medical help or contact a Poison Control Center right away.

Directions

Open package, remove one wet wipe to clean your hands and body. Reseal, keep closed to prevent evaporation.

Allow to dry without wiping. Discard propearly after use.

Supervise children under 6 years of age when using this product to avoid swallowing.

Other information

Store at room temperature

Do not flush down toilet.

Inactive ingredients

Water, Glycerin, Aloe barbadensis Extract.